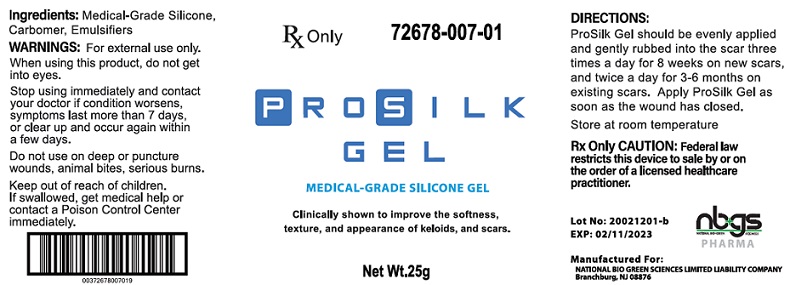 DRUG LABEL: PROSILK MEDICAL GRADE SILICONE SCAR GEL
NDC: 72678-007
Manufacturer: NATIONAL BIO GREEN SCIENCES LIMITED LIABILITY COMPANY
Category: other | Type: MEDICAL DEVICE
Date: 20200714
INACTIVE INGREDIENTS: CYCLOMETHICONE 5; DIMETHICONE CROSSPOLYMER (450000 MPA.S AT 12% IN CYCLOPENTASILOXANE); DIMETHICONOL (2000 CST); DIMETHICONE; CYCLOMETHICONE 4; SILICON; STEARYL ALCOHOL

ProSilk Gel Pump

ProSilk Gel Pump
----------------------------
NATIONAL BIO GREEN SCIENCES LIMITED LIABILITY COMPANY
Rx only
For external use only
Not for ophthalmic use

DESCRIPTION

ProSilk Gel is intended for use in the management of closed hyperproliferative scars, both old and new hypertrophic or keloid scars resulting from burns, surgical procedures or trauma wounds. It helps reduce redness, softens and flattens raised scars, relieves itching, discomfort and pain associated with scars, helps prevent excessive and abnormal scar formation, and for use as mono-therapy or in combination with other scar therapies including pressure garments.

ProSilk Gel is a self-drying, flexible, gas permeable, waterproof silicone gel that is colorless and odorless. ProSilk Gel forms a bond with the stratum corneum (the outer layer of dead skin cells) forming a protective barrier against chemical physical and microbial invasion of the scar site while assisting with hydration.

ProSilk Gel is also for use on children or people with sensitive skin. Silicone gel and sheets are internationally recommended as the first line of treatment in scar management.

INGREDIENTS

ProSilk Gel contains: Cyclopentasiloxane, Bis-Vinyl Dimethicone/Dimethicone Copolymer, Dimethiconol, Dimethicone, Cyclotetrasiloxane, Silicon, Steraryl Alcohol.

CLINCIAL PHARMACOLOGY

The exact mechanism of action in improving the appearance of scar tissue from using silicone remains unknown. However, various suggestions have been made to explain the efficacy of silicone, including hydration, pressure, temperature, oxygen transmission and silicone absorption. There is some evidence that the treatment affects the stratum corneum and, by reducing evaporation, restores better homeostasis in the tissue. In keloid and hypertrophic scarring, the stratum corneum allows more evaporation of water from the underlying tissue than occurs in normal skin. Silicone may prevent this, keeping the stratum corneum in optimal hydration and protecting the skin from environmental hazards, both of which can reduce abnormal scarring. The gel may also affect the stratum corneum by inhibiting mast cell activity, diminishing edema, vasodilatation and excessive extracellular matrix formation but the simple changes in temperature, pressure, oxygen tension and hydration produced by wound coverage probably constitute the main mechanism of action. Another hypothesis is that the effect of static electricity on silicone may influence the alignment of collagen deposition.

INDICATIONS AND USES

For use in the management of closed hyperproliferative (hypertrophic or keloid) scars, resulting from general surgical procedures, trauma, wounds, and burns.

CONTRAINDICATIONS

ProSilk Gel is contraindicated in patients with known hypersensitivity to silicone or any of the listed ingredients.

WARNINGS

For external use only. Avoid direct contact with eyes, lips or mucous membranes. Do not apply on areas of broken skin. Do not apply on third degree burns and open wounds. Never use on sutured wound until sutures have been removed. Do not use on dermatological conditions that disrupt the integrity of the skin.

PRECAUTIONS

Stop use and ask a doctor if irritation develops. In rare instances, silicone gel may cause a rash on the skin. This condition may result from improper cleansing of the scar area where the silicone gel has been applied. If this product is applied properly and skin irritation still occurs, discontinue use and consult your physician. If ingested, get medical help or contact Poison Control Center right away.

KEEP THIS AND ALL MEDICATION OUT OF THE REACH OF CHILDREN.

This medication should be used as directed by your physician during pregnancy or while breastfeeding. Consult your doctor about the risks and benefits.

CAUTION: Federal law restricts this device to sale by or on the order of a physician.

ADVERSE REACTIONS

On rare occasions, the gel may cause temporary redness, stinging, burning or irritation and normally disappear when the medication is discontinued.

DOSAGE AND ADMINISTRATION

1. Ensure that the affected area is clean and dry.
2. Apply ProSilk Gel to the area as a very thin coat and allow to dry.
3. Apply ProSilk Gel twice a day
4. Once dry, ProSilk Gel can be covered with cosmetics or sunscreen.
5. Recommended duration of treatment is 60-90 days.

How is the Product Supplied

ProSilk Gel is supplied in:

25 gram Pump

Store at 20°-25°C (68° to 77°F); Keep away from heat and protect from freezing. [See USP Controlled Room Temperature.]

Manufactured for:

NATIONAL BIO GREEN SCIENCES LIMITED LIABILITY COMPANY